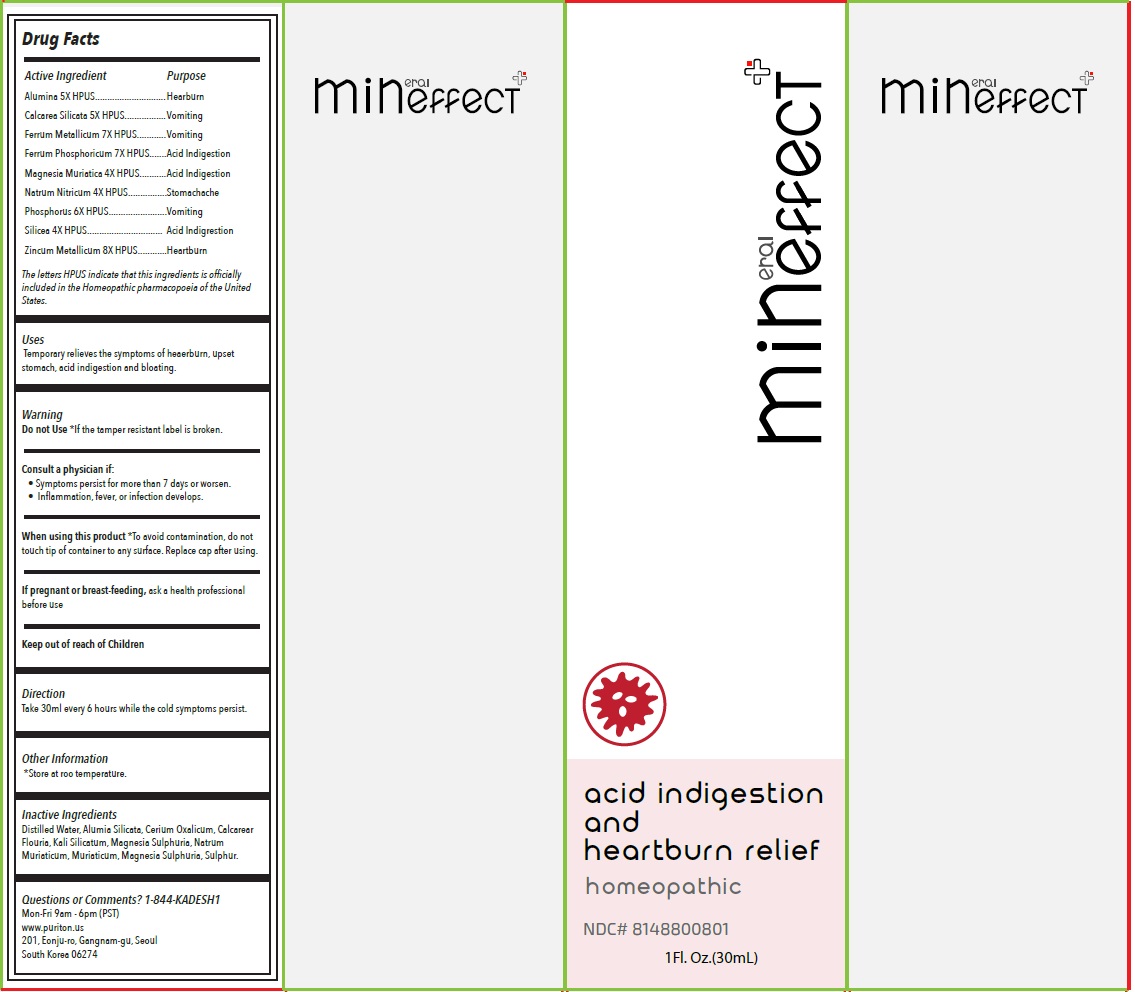 DRUG LABEL: Mineffect acid indigestion and heartburn relief
NDC: 81488-008 | Form: LIQUID
Manufacturer: Kadesh Incoporation Co,Ltd
Category: homeopathic | Type: HUMAN OTC DRUG LABEL
Date: 20231031

ACTIVE INGREDIENTS: ALUMINUM OXIDE 5 [hp_X]/30 mL; CALCIUM SILICATE 5 [hp_X]/30 mL; IRON 7 [hp_X]/30 mL; FERROSOFERRIC PHOSPHATE 7 [hp_X]/30 mL; MAGNESIUM CHLORIDE 4 [hp_X]/30 mL; SODIUM NITRATE 4 [hp_X]/30 mL; PHOSPHORUS 6 [hp_X]/30 mL; SILICON DIOXIDE 4 [hp_X]/30 mL; ZINC 8 [hp_X]/30 mL
INACTIVE INGREDIENTS: WATER; KAOLIN; CEROUS OXALATE NONAHYDRATE; CALCIUM FLUORIDE; POTASSIUM SILICATE; MAGNESIUM SULFATE HEPTAHYDRATE; SODIUM CHLORIDE; SULFUR

Mineffect acid indigestion and heartburn relief

Active Ingredient

Alumina 5X HPUS
Calcarea Silicata 5X HPUS
Ferrum Metallicum 7X HPUS
Ferrum Phosphoricum 7X HPUS
Magnesia Muriatica 4X HPUS
Natrum Nitricum 4X HPUS
Phosphorus 6X HPUS
Silicea 4X HPUS
Zincum Metallicum 8X HPUS

The letters HPUS indicate that this ingredients is officially included in the Homeopathic pharmacopoeia of the United States.

Purpose

Heartburn
Vomiting
Vomiting
Acid Indigestion
Acid Indigestion
Stomachache
Vomiting
Acid Indigestion
Heartburn

Uses

Temporary relieves the symptoms of heartburn, upset stomach, acid indigestion and bloating.

Warning

Do not Use*If the tamper resistant label is broken.

Consult a physician if:
• Symptoms persist for more than 7 days or worsen.
• Inflammation, fever, or infection develops.

When using this product *To avoid contamination, do not touch tip of container to any surface. Replace cap after using.

If pregnant or breast-feeding,ask a health professional before use

Keep out of reach of Children

Direction

Take 30 ml every 6 hours while the acid indigestion symptoms persist.

Other Information

*Store at room temperature.

Inactive Ingredients

Distilled water, Alumina Silicata, Cerium Oxalicum, Calcarea Fluorica, Kali Silicatum, Magnesia Sulphurica, Natrum Muriaticum, Sulphur.

Questions or Comments?

1-844-KADESH1
Mon-Fri 9am - 6pm (PST)
www.puriton.us
201, Eonju-ro, Gangnam-gu, Seoul
South Korea 06274

homeopathic